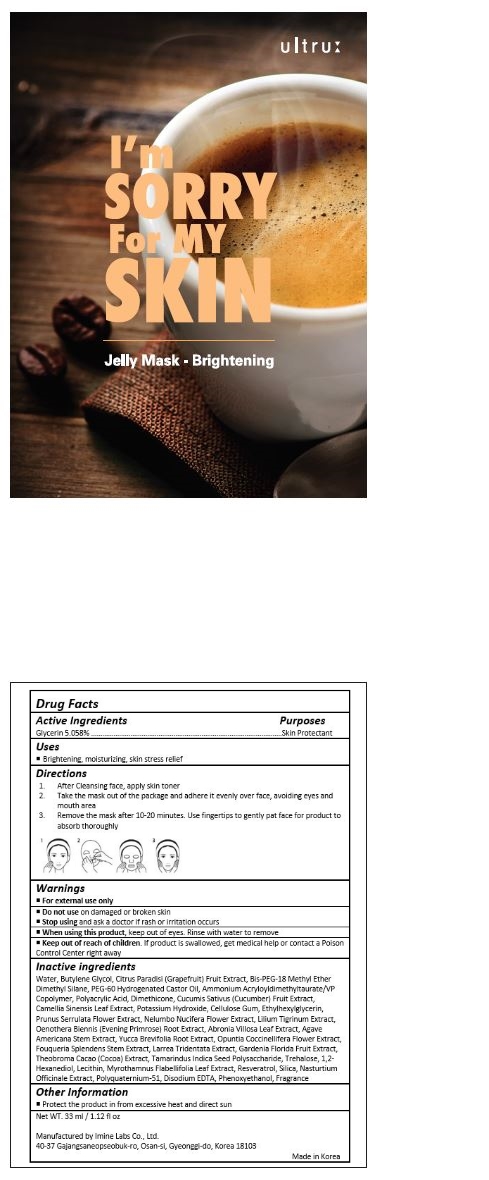 DRUG LABEL: IM SORRY FOR MY SKIN MASK - BRIGHTENING
NDC: 70687-001 | Form: CREAM
Manufacturer: IMINELABS
Category: otc | Type: HUMAN OTC DRUG LABEL
Date: 20160517

ACTIVE INGREDIENTS: GLYCERIN 1.67 mg/33 mL
INACTIVE INGREDIENTS: WATER; BUTYLENE GLYCOL; GRAPEFRUIT; BIS-PEG-18 METHYL ETHER DIMETHYL SILANE; PEG-60 HYDROGENATED CASTOR OIL; AMMONIUM ACRYLOYLDIMETHYLTAURATE/VP COPOLYMER; POLYACRYLIC ACID (250000 MW); DIMETHICONE; CUCUMBER; GREEN TEA LEAF; POTASSIUM HYDROXIDE; CARBOXYMETHYLCELLULOSE SODIUM, UNSPECIFIED FORM; ETHYLHEXYLGLYCERIN; PRUNUS SERRULATA FLOWER; NELUMBO NUCIFERA FLOWER; LILIUM LANCIFOLIUM BULB; OENOTHERA BIENNIS ROOT; ABRONIA VILLOSA LEAF; AGAVE AMERICANA STEM; YUCCA BREVIFOLIA ROOT; OPUNTIA COCHENILLIFERA FLOWER; FOUQUIERIA SPLENDENS STEM; LARREA TRIDENTATA WHOLE; GARDENIA JASMINOIDES FRUIT; COCOA; TREHALOSE; 1,2-HEXANEDIOL; EGG PHOSPHOLIPIDS; MYROTHAMNUS FLABELLIFOLIA LEAF; RESVERATROL; SILICON DIOXIDE; NASTURTIUM OFFICINALE; POLYQUATERNIUM-51 (2-METHACRYLOYLOXYETHYL PHOSPHORYLCHOLINE/N-BUTYL METHACRYLATE; 3:7); EDETATE DISODIUM; PHENOXYETHANOL

Drug Facts

ACTIVE INGREDIENT

Glycerin 5.058%

PURPOSE

Skin Protectant

INDICATIONS AND USAGE

Brightening, moisturizing, skin stress relief

DOSAGE AND ADMINISTRATION

1. After Cleansing face, apply skin toner
2. Take the mask out of the package and adhere it evenly over face, avoiding eyes and mouth area
3. Remove the mask after 10-20 minutes. Use fingertips to gently pat face for product to absorb thoroughly

WARNINGS

For external use only.
Do not use on damaged or broken skin.
When using this product, keep out of eyes. Rinse with water to remove
Stop using and ask a doctor if rash occurs.

Keep out of reach of children.

If product is swallowed, get medical help or contact a Poison Control Center right away.

INACTIVE INGREDIENT

Water, Butylene Glycol, Citrus Paradisi (Grapefruit) Fruit Extract, Bis-PEG-18 Methyl Ether Dimethyl Silane, PEG-60 Hydrogenated Castor Oil, Ammonium Acryloyldimethyltaurate/VP Copolymer, Polyacrylic Acid, Dimethicone, Cucumis Sativus (Cucumber) Fruit Extract, Camellia Sinensis Leaf Extract, Potassium Hydroxide, Cellulose Gum, Ethylhexylglycerin, Prunus Serrulata Flower Extract, Nelumbo Nucifera Flower Extract, Lilium Tigrinum Extract, Oenothera Biennis (Evening Primrose) Root Extract, Abronia Villosa Leaf Extract, Agave Americana Stem Extract, Yucca Brevifolia Root Extract, Opuntia Coccinellifera Flower Extract, Fouqueria Splendens Stem Extract, Larrea Tridentata Extract, Gardenia Florida Fruit Extract, Theobroma Cacao (Cocoa) Extract, Tamarindus Indica Seed Polysaccharide, Trehalose, 1,2-Hexanediol, Lecithin, Myrothamnus Flabellifolia Leaf Extract, Resveratrol, Silica, Nasturtium Officinale Extract, Polyquaternium-51, Disodium EDTA, Phenoxyethanol, Fragrance